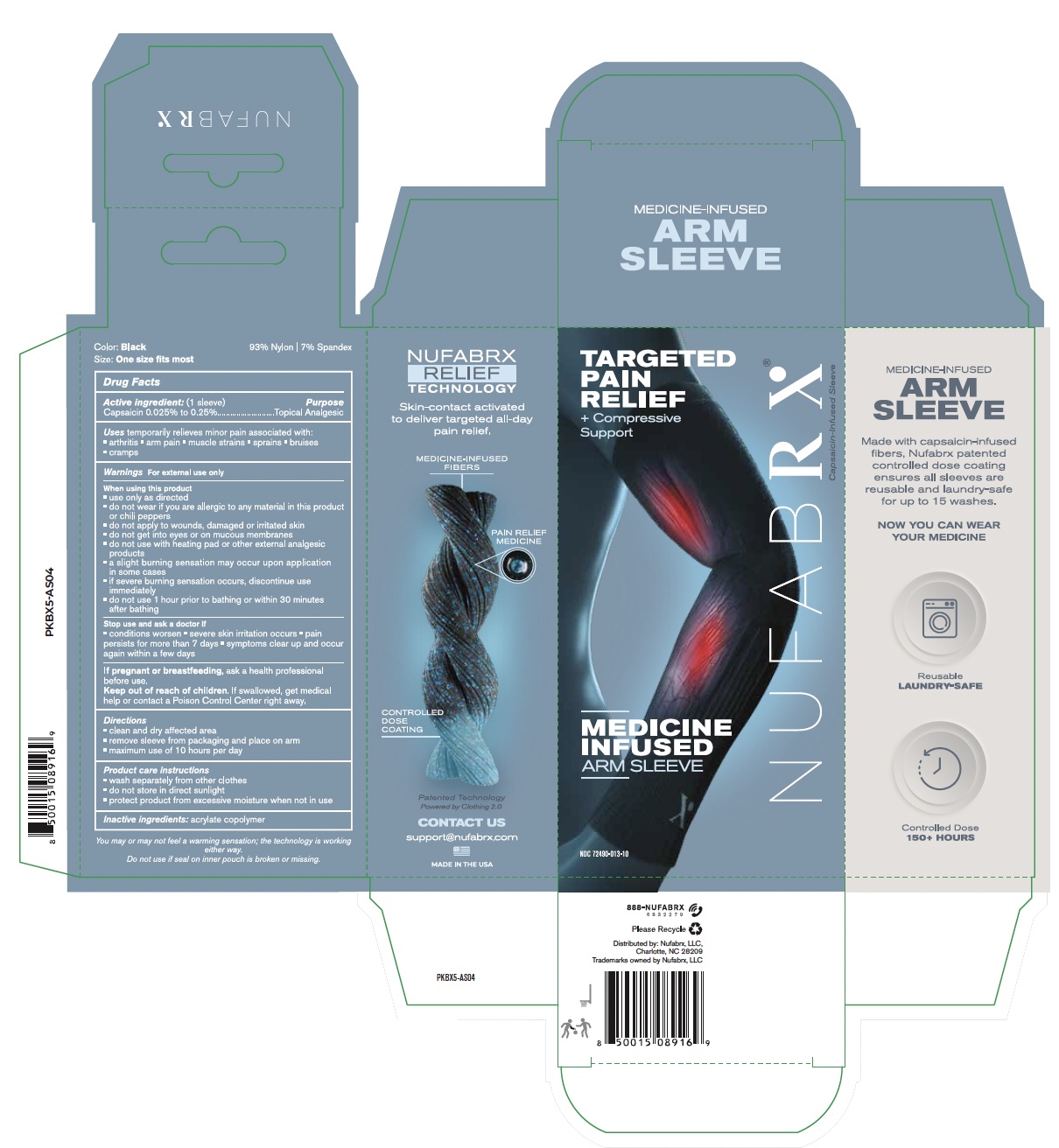 DRUG LABEL: Nufabrx Arm Sleeve
NDC: 72490-013 | Form: CLOTH
Manufacturer: Nufabrx LLC
Category: otc | Type: HUMAN OTC DRUG LABEL
Date: 20251015

ACTIVE INGREDIENTS: CAPSAICIN 0.2 g/100 g
INACTIVE INGREDIENTS: BUTYL ACRYLATE/METHYL METHACRYLATE/METHACRYLIC ACID COPOLYMER (18000 MW)

72490-013 Nufabrx Arm Sleeve

Active Ingredient

Synthetic Capsaicin 0.20%

Purpose

Topical Analgesic

Uses

For the temporary relief of minor aches and pains of muscles and joints associated with: simple backache, arthritis, strains, bruises, and sprains.

Warnings

For external use only

Do not use

- Allergy Alert: if you are allergic to any ingredients of this product or chili peppers contact a doctor before use
- On wounds or to damaged skin
- With, or at same time as, other analgesic products
- With a heating pad

When using this product

- You may experience a burning sensation which is normal and related to the way the product works. With regular use, this sensation generally diminishes.
- Do not use immediately before or after activities such as swimming, showering, or sunbathing
- Use only as directed.
- Avoid contact with eyes and mucous membranes or rashes.
- Wash hands after putting product on body and before touching your face or eyes.

Stop use and ask a doctor if

- condition worsens, symptoms persist more than 7 days or clear up and occur again within a few days
- rash, itching or excessive skin irritation develops
- If pregnant or breastfeeding consult a healthcare professional before use.

Keep out of reach of children.

If swallowed, get medical help or contact a Poison Control Center right away.

Directions

- Clean and dry affected area
- Remove product and put on body
- Maximum use of 8 hours per day
- Do not wear more than 4 days per week without doctor consent
- Wash separately for best results

Other Information

Avoid storing product in direct sunlight. Protect product from excessive moisture

Inactive Ingredients

Acrylate Copolymer